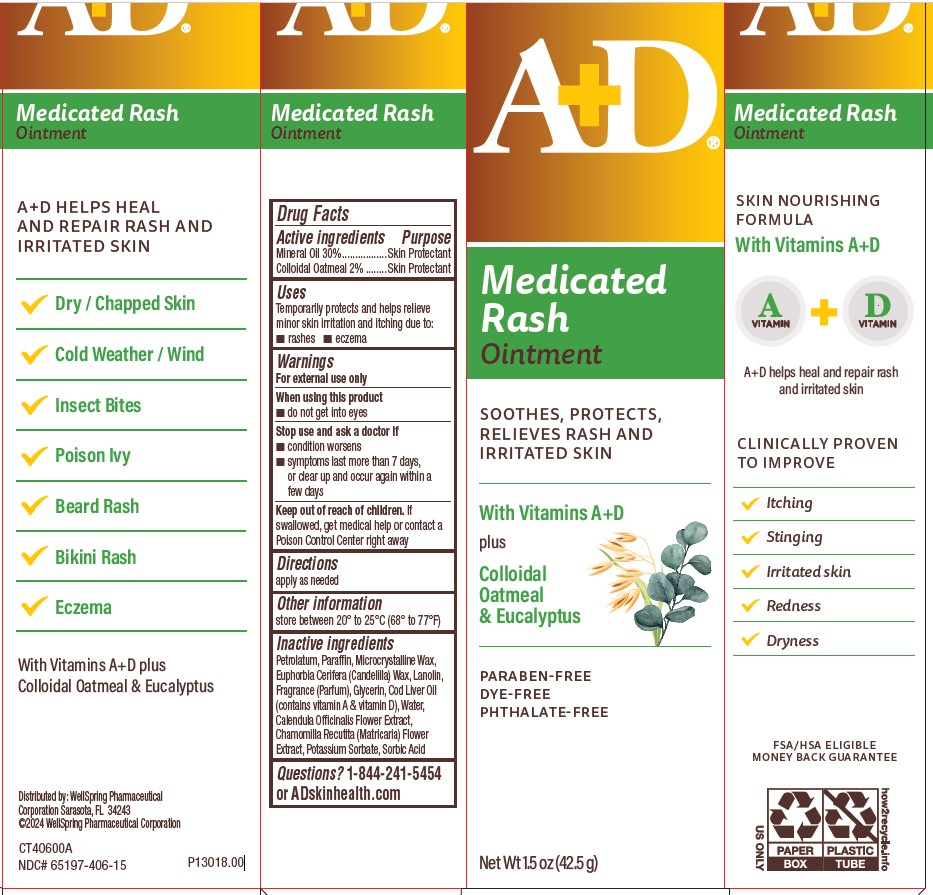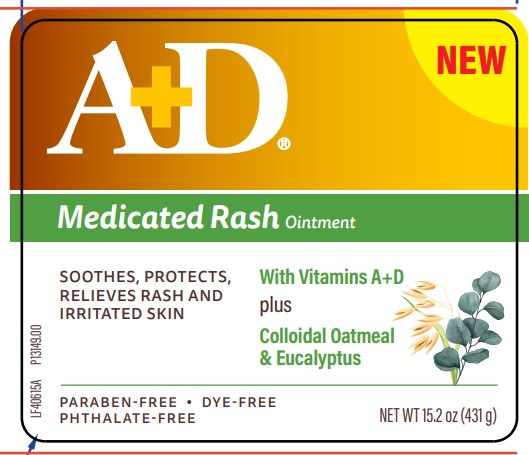 DRUG LABEL: AD Medicated Rash
NDC: 65197-406 | Form: OINTMENT
Manufacturer: WellSpring Pharmaceutical Corporation
Category: otc | Type: HUMAN OTC DRUG LABEL
Date: 20241227

ACTIVE INGREDIENTS: MINERAL OIL 30 g/100 g; OATMEAL 2 g/100 g
INACTIVE INGREDIENTS: PETROLATUM; PARAFFIN; MICROCRYSTALLINE WAX; CANDELILLA WAX; LANOLIN; GLYCERIN; COD LIVER OIL; WATER; CALENDULA OFFICINALIS FLOWER; CHAMOMILE; POTASSIUM SORBATE; SORBIC ACID

A+D Medicated Rash Ointment

Active Ingredients

Mineral Oil 30%

Colloidal Oatmeal 2%

Purpose

Skin protectant

Skin protectant

Uses

Temporarily protects and helps relieve minor skin irritation and itching due to:

- rashes
- eczema

Warnings

For external use only

When using this product

- do not get into eyes

Stop use and ask a doctor if

- condition worsens
- symptoms persist for more than 7 days, or clear up and occur again within a few days

Keep out of reach of children

If swallowed, get medical help or contact a Poison Control Center right away.

Directions

- apply as needed

Other information

store between 20° to 25°C (68° to 77°F)

Inactive ingredients

Petrolatum, Paraffin, Microcrystalline Wax, Euphorbia Cerifera (Candelilla) Wax, Lanolin,Fragrance (Parfum), Glycerin, Cod Liver Oil (contains vitamin A & vitamin D), Water,
Calendula Officinalis Flower Extract, Chamomilla Recutita (Matricaria) Flower Extract, Potassium Sorbate, Sorbic Acid.

Questions?

1-844-241-5454 or ADskinhealth.com

Distributed by:

WellSpring Pharmaceutical Corporation
Sarasota, FL 34243

© 2024 WellSpring Pharmaceutical Corporation

PACKAGE LABEL. PRINCIPAL DISPLAY PANEL 65197-406-15

A+D MEDICATED RASH OINTMENT 1.5oz

A+D Medicated Rash Ointment

SOOTHES, PROTECTS, RELIEVES RASH AND IRRITATED SKIN

WITH VITAMIN A & VITAMIN D plus COLLOIDAL OATMEAL & EUCALYPTUS

PARABEN-FREE
DYE-FREE
PHTHALATE-FREE

NET WT 1.5 OZ (42.5g)

Skin nourishing formula with Vitamin A and Vitamin D

helps heal and moisturize irritated skin

CLINICALLY PROVEN TO IMPROVE:

Itching

Stinging

Irritated Skin

Redness

Dryness

CT40600A

P13018.00

NDC# 65197-406-15

UPC: 365197406005

65197-406-52

A+D Medicated Rash Ointment 15.2 oz
65197-406-52